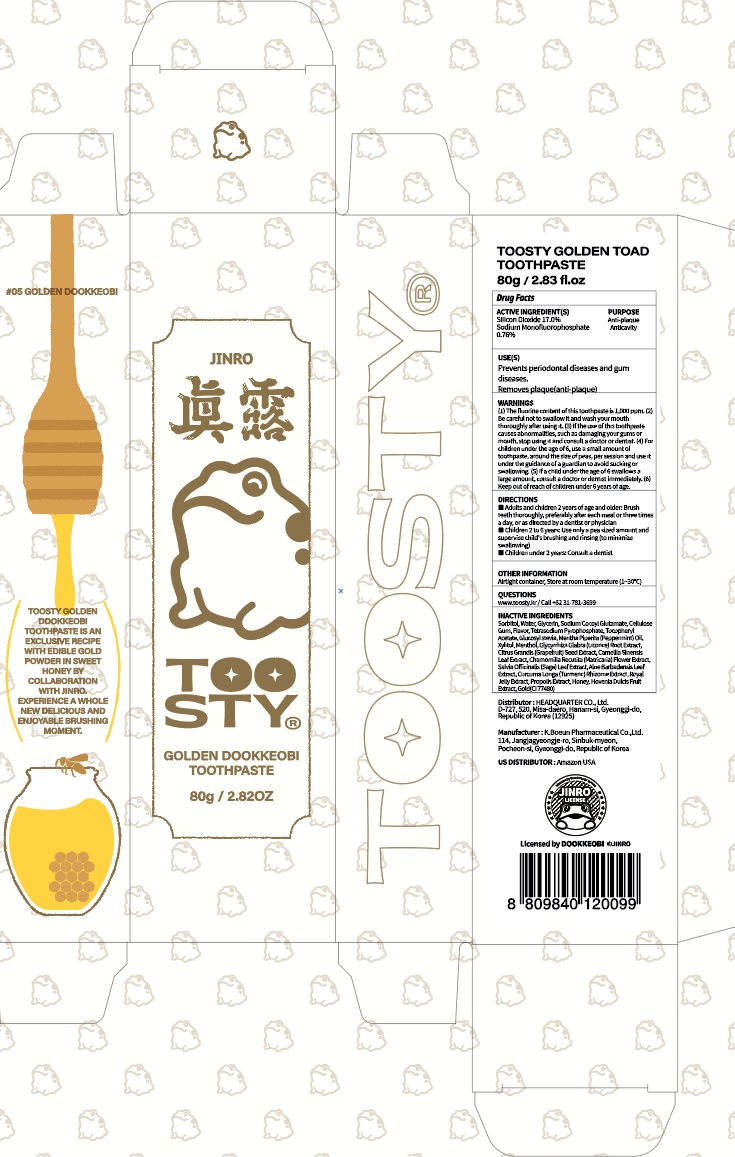 DRUG LABEL: TOOSTY GOLDEN TOAD TOOTHPASTE
NDC: 82662-070 | Form: PASTE, DENTIFRICE
Manufacturer: Headquarter Co., Ltd
Category: otc | Type: HUMAN OTC DRUG LABEL
Date: 20240228

ACTIVE INGREDIENTS: Sodium Monofluorophosphate 0.76 g/100 g; SILICON DIOXIDE 17.0 g/100 g
INACTIVE INGREDIENTS: SORBITOL; Water; Glycerin

ACTIVE INGREDIENTS

Silicon Dioxide 17.0%
Sodium Monofluorophosphate 0.76%

INACTIVE INGREDIENTS

Sorbitol, Water, Glycerin, Sodium Cocoyl Glutamate, Cellulose Gum, Flavor, Tetrasodium Pyrophosphate, Tocopheryl Acetate, Glucosyl stevia, Mentha Piperita (Peppermint) Oil, Xylitol, Menthol, Glycyrrhiza Glabra (Licorice) Root Extract, Citrus Grandis (Grapefruit) Seed Extract, Camellia Sinensis Leaf Extract, Chamomilla Recutita (Matricaria) Flower Extract, Salvia Officinalis (Sage) Leaf Extract, Aloe Barbadensis Leaf Extract, Curcuma Longa (Turmeric) Rhizome Extract, Royal Jelly Extract, Propolis Extract, Honey, Hovenia Dulcis Fruit Extract, Gold(CI 77480)

PURPOSE

Anti-plaque
Anticavity

WARNINGS

(1) The fluorine content of this toothpaste is 1,000 ppm. (2) Be careful not to swallow it and wash your mouth thoroughly after using it. (3) If the use of this toothpaste causes abnormalities, such as damaging your gums or mouth, stop using it and consult a doctor or dentist. (4) For children under the age of 6, use a small amount of toothpaste, around the size of peas, per session and use it under the guidance of a guardian to avoid sucking or swallowing. (5) If a child under the age of 6 swallows a large amount, consult a doctor or dentist immediately. (6) Keep out of reach of children under 6 years of age.

Keep out of reach of children under the age of 6

Uses

Prevents periodontal diseases and gum diseases.
Removes plaque(anti-plaque)

Directions

■ Adults and children 2 years of age and older: Brush teeth thoroughly, preferably after each meal or three times a day, or as directed by a dentist or physician
■ Children 2 to 6 years: Use only a pea sized amount and supervise child's brushing and rinsing (to minimize swallowing)
■ Children under 2 years: Consult a dentist

Other Information

■ Airtight container, Store at room temperature (1~30℃)

Questions

■ www.toosty.kr / Call +82 31-781-3699